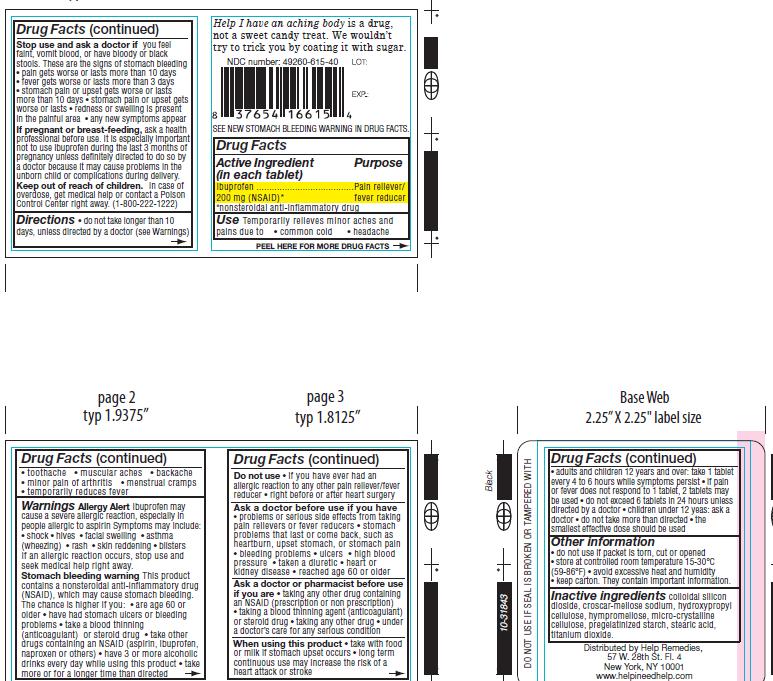 DRUG LABEL: Help I Have an Aching Body
NDC: 49260-615 | Form: TABLET
Manufacturer: Help Remedies, Inc.
Category: otc | Type: HUMAN OTC DRUG LABEL
Date: 20130305

ACTIVE INGREDIENTS: IBUPROFEN 200 mg/1 1
INACTIVE INGREDIENTS: SILICON DIOXIDE; CROSCARMELLOSE SODIUM; HYDROXYPROPYL CELLULOSE; HYPROMELLOSES; CELLULOSE, MICROCRYSTALLINE; STARCH, CORN; STEARIC ACID; TITANIUM DIOXIDE

Drug Facts

Active Ingredient..................................................Purpose
(in each tablet)

Ibuprofen 200 mg (NSAID)*.....................................Pain reliever/ Fever reducer
*nonsteroidal anti-inflammatory drug

Use

Temporarily relieves minor aches and pains due to • common cold • headache
• toothache • muscular aches • backache • minor pain of arthritis • menstrual cramps
• temporarily reduces fever

Warnings
Allergy Alert Ibuprofen may cause a severe allergic reaction, especially in people allergic to aspirin Symptoms may include:
• shock • hives • facial swelling • asthma (wheezing) • rash • skin reddening • blisters If an allergic reaction occurs, stop use and
seek medical help right away. Stomach bleeding warning This product contains a nonsteroidal anti-inflammatory drug (NSAID), which may cause stomach bleeding. The chance is higher if you: • are age 60 or older • have had stomach ulcers or bleeding problems • take a blood thinning (anticoagulant) or steroid drug • take other drugs containing an NSAID (aspirin, ibuprofen, naproxen or others) • have 3 or more alcoholic drinks every day while using this product • take more or for a longer time than directed.
Stop use and ask a doctor if you feel faint, vomit blood, or have bloody or black stools. These are the signs of stomach bleeding
• pain gets worse or lasts more than 10 days • fever gets worse or lasts more than 3 days • stomach pain or upset gets worse or lasts
more than 10 days • stomach pain or upset gets worse or lasts • redness or swelling is present in the painful area • any new symptoms appear.
Ask a doctor before use if you have • problems or serious side effects from taking pain relievers or fever reducers • stomach
problems that last or come back, such as heartburn, upset stomach, or stomach pain • bleeding problems • ulcers • high blood
pressure • taken a diuretic • heart or kidney disease • reached age 60 or older.
Ask a doctor or pharmacist before use if you are • taking any other drug containing an NSAID (prescription or non prescription)
• taking a blood thinning agent (anticoagulant) or steroid drug • taking any other drug • under a doctor’s care for any serious condition.

Do not use

• if you have ever had an allergic reaction to any other pain reliever/fever reducer

• right before or after heart surgery

Keep out of reach of children. In case of overdose, get medical help or contact a Poison
Control Center right away. (1-800-222-1222)

PREGNANCY OR BREAST FEEDING

If pregnant or breast-feeding, ask a health professional before use. It is especially important not to use ibuprofen during the last 3 months of pregnancy unless definitely directed to do so by a doctor because it may cause problems in the unborn child or complications during delivery.

When using this product
• take with food or milk if stomach upset occurs • long term continuous use may increase the risk of a heart attack or stroke.
Adults and children 12 years and over: take 1 tablet every 4 to 6 hours while symptoms persist
• if pain or fever does not respond to 1 tablet, 2 tablets may be used
• do not exceed 6 tablets in 24 hours unless directed by a doctor
• children under 12 yeas: ask a doctor • do not take more than directed
• the smallest effective dose should be used

Directions
• do not take longer than 10 days, unless directed by a doctor (see Warnings)
Other information
• do not use if packet is torn, cut or opened
• store at controlled room temperature 15-30°C (59-86°F) • avoid excessive heat and humidity
• keep carton. They contain important information.

QUESTIONS

Distributed by Help Remedies,
57 W. 28th St. Fl. 4
New York, NY 10001

www.helpineedhelp.com

Inactive ingredients

colloidal silicon dioxide, croscar-mellose sodium, hydroxypropyl
cellulose, hympromellose, micro-crystalline
cellulose, pregelatinized starch, stearic acid,
titanium dioxide.